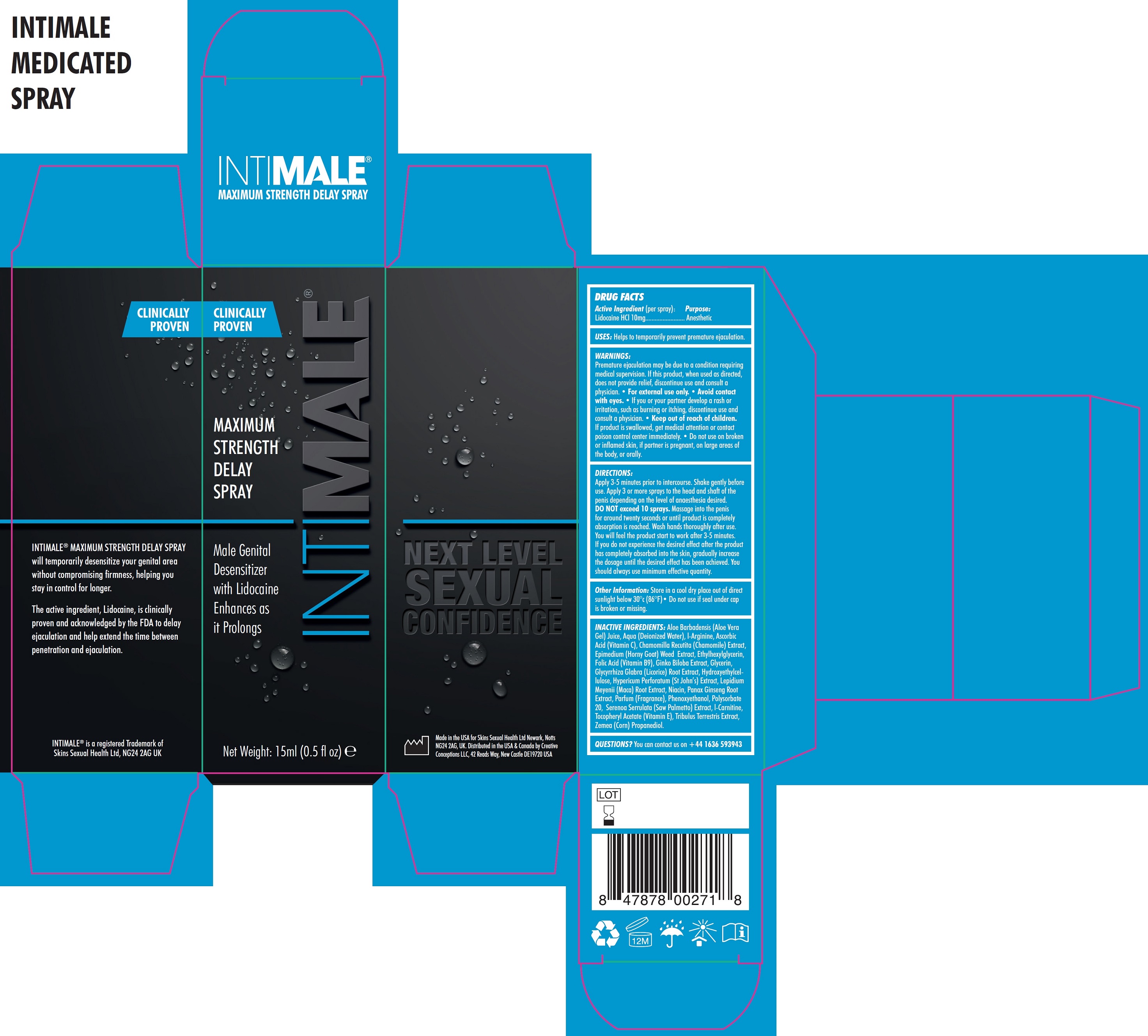 DRUG LABEL: INTIMALE Maximum Strength Delay
NDC: 81923-197 | Form: SOLUTION
Manufacturer: SKINS SEXUAL HEALTH LIMITED
Category: otc | Type: HUMAN OTC DRUG LABEL
Date: 20231111

ACTIVE INGREDIENTS: LIDOCAINE HYDROCHLORIDE 10 mg/1 mL
INACTIVE INGREDIENTS: ALOE VERA LEAF; WATER; ARGININE; ASCORBIC ACID; CHAMOMILE; EPIMEDIUM GRANDIFLORUM TOP; ETHYLHEXYLGLYCERIN; FOLIC ACID; GINKGO; GLYCERIN; GLYCYRRHIZA GLABRA; HYDROXYETHYL CELLULOSE, UNSPECIFIED; HYPERICUM PERFORATUM WHOLE; LEPIDIUM MEYENII ROOT; NIACIN; ASIAN GINSENG; PHENOXYETHANOL; POLYSORBATE 20; SAW PALMETTO; LEVOCARNITINE; .ALPHA.-TOCOPHEROL ACETATE; TRIBULUS TERRESTRIS WHOLE; CORN

INTIMALE Maximum Strength Delay Spray

(per spray): Active Ingredient

Lidocaine HCL 10mg

Purpose:

Anesthetic

USES:

Helps to temporarily prevent premature ejaculation.

WARNINGS:

Premature ejaculation may be due to a condition requiring medical supervision. If this product, when used as directed, does not provide relief, discontinue use and consult a physician.

- For external use only.
- Avoid contact with eyes.
- If you or your partner develop a rash or irritation, such as burning or itching, discontinue use and consult a physician.

Keep out of reach of children.

- If product is swallowed, get medical attention or contact poison control center immediately.

Do not use

- on broken or inflamed skin, if partner is pregnant, on large areas of the body, or orally.

DIRECTIONS:

Apply 3-5 minutes prior to intercourse. Shake gently before use. Apply 3 or more sprays to the head and shaft of the penis depending on the level of anaesthesia desired. exceed Massage into the penis for around twenty seconds or until product is completely absorption is reached. Wash hands thoroughly after use. You will feel the product start to work after 3-5 minutes. If you do not experience the desired effect after the product has completely absorbed into the skin, gradually increase the dosage until the desired effect has been achieved. You should always use minimum effective quantity. DO NOT 10 sprays.

Other Information:

Store in a cool dry place out of direct sunlight below 30°c (86°F)• Do not use if seal under cap is broken or missing.

INACTIVE INGREDIENTS:

Aloe Barbadensis (Aloe Vera Gel) Juice, Aqua (Deionized Water), l-Arginine, Ascorbic Acid (Vitamin C), Chamomilla Recutita (Chamomile) Extract, Epimedium (Horny Goat) Weed Extract, Ethylhexylglycerin, Folic Acid (Vitamin B9), Ginko Biloba Extract, Glycerin, Glycyrrhiza Glabra (Licorice) Root Extract, Hydroxyethylcellulose, Hypericum Perforatum (St John’s) Extract, Lepidium Meyenii (Maca) Root Extract, Niacin, Panax Ginseng Root Extract, Parfum (Fragrance), Phenoxyethanol, Polysorbate 20, Serenoa Serrulata (Saw Palmetto) Extract, l-Carnitine, Tocopheryl Acetate (Vitamin E), Tribulus Terrestris Extract, Zemea (Corn) Propanediol.

QUESTIONS?

You can contact us on +44 1636 593943